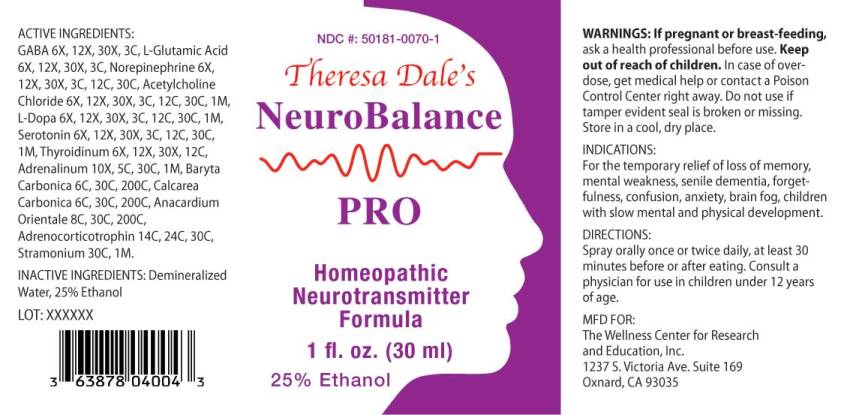 DRUG LABEL: Neurobalance Pro
NDC: 50181-0070 | Form: LIQUID
Manufacturer: The Wellness Center for Reseach and Education, Inc.
Category: homeopathic | Type: HUMAN OTC DRUG LABEL
Date: 20250606

ACTIVE INGREDIENTS: .GAMMA.-AMINOBUTYRIC ACID 6 [hp_X]/1 mL; GLUTAMIC ACID 6 [hp_X]/1 mL; NOREPINEPHRINE BITARTRATE 6 [hp_X]/1 mL; ACETYLCHOLINE CHLORIDE 6 [hp_X]/1 mL; LEVODOPA 6 [hp_X]/1 mL; SEROTONIN HYDROCHLORIDE 6 [hp_X]/1 mL; THYROID 6 [hp_X]/1 mL; EPINEPHRINE 10 [hp_X]/1 mL; BARIUM CARBONATE 6 [hp_C]/1 mL; OYSTER SHELL CALCIUM CARBONATE, CRUDE 6 [hp_C]/1 mL; SEMECARPUS ANACARDIUM JUICE 8 [hp_C]/1 mL; CORTICOTROPIN 14 [hp_C]/1 mL; DATURA STRAMONIUM 30 [hp_C]/1 mL
INACTIVE INGREDIENTS: WATER; ALCOHOL

Drug Facts:

ACTIVE INGREDIENTS:

GABA (Gamma-Aminobutyric Acid) 6X, 12X, 30X, 3C, L-Glutamic Acid 6X, 12X, 30X, 3C, Norepinephrine (Bitartrate) 6X, 12X, 30X, 3C, 12C, 30C, Acetylcholine Chloride 6X, 12X, 30X, 3C, 12C, 30C, 1M, L-Dopa 6X, 12X, 30X, 3C, 12C, 30C, 1M, Serotonin (Hydrochloride) 6X, 12X, 30X, 3C, 12C, 30C, 1M, Thyroidinum (Suis) 6X, 12X, 30X 12C, Adrenalinum 10X, 5C, 30C, 1M, Baryta Carbonica 6C, 30C, 200C, Calcarea Carbonica 6C, 30C, 200C, Anacardium Orientale 8C, 30C, 200C, Adrenocorticotrophin 14C, 24C, 30C, Stramonium 30C, 1M.

INDICATIONS:

For the temporary relief of loss of memory, metal weakness, senile dementia, forgetfulness, confusion, anxiety, brain fog, children with slow mental and physical development.

WARNINGS:

If pregnant or breast-feeding, ask a health professional before use.

Keep out of reach of children. In case of overdose, get medical help or contact a Poison Control Center right away.

Do not use if tamper evident seal is broken or missing.

Store in a cool, dry place.

Keep out of reach of children. In case of overdose, get medical help or contact a Poison Control Center right away.

DIRECTIONS:

Spray orally once or twice daily, at least 30 minutes before or after eating. Consult a physician for use in children under 12 years of age.

INDICATIONS:

For the temporary relief of loss of memory, metal weakness, senile dementia, forgetfulness, confusion, anxiety, brain fog, children with slow mental and physical development.

INACTIVE INGREDIENTS:

Demineralized Water, 25% Ethanol

QUESTIONS:

MFD FOR:

The Wellness Center for Research

and Education, Inc.

1237 S. Victoria Ave. Suite 169

Oxnard, CA 93035

PACKAGE DISPLAY LABEL:

NDC#: 50181-0070-1

Theresa Dale's

NeuroBalance

PRO

Homeopathic

Neurotransmitter

Formula

1 fl. oz. (30 ml)